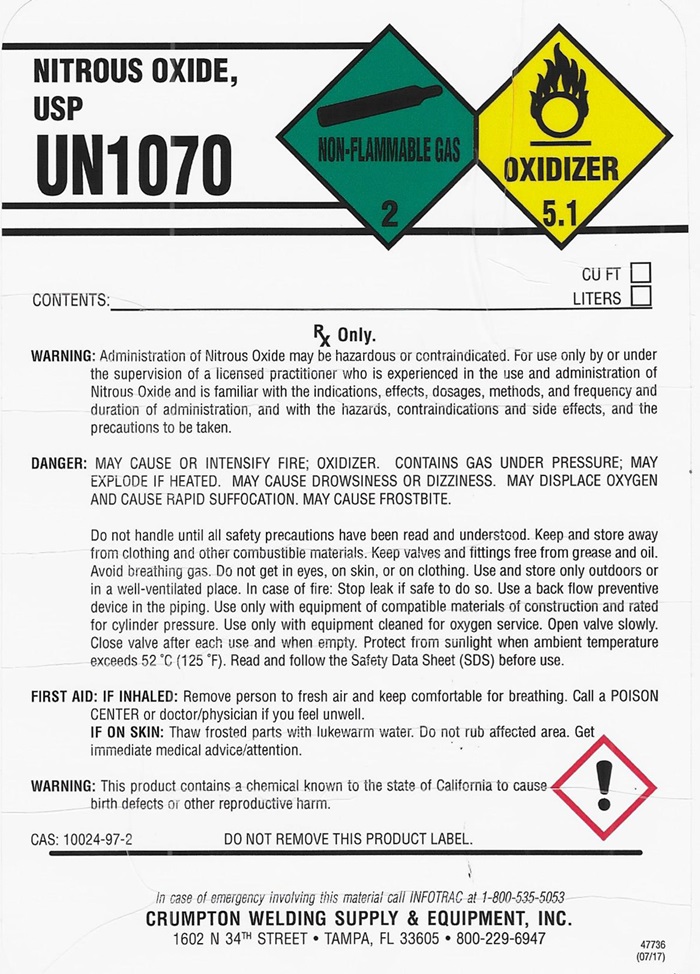 DRUG LABEL: NITROUS OXIDE
NDC: 52568-002 | Form: GAS
Manufacturer: Crumpton Welding Supply & Equipment, Inc.
Category: prescription | Type: HUMAN PRESCRIPTION DRUG LABEL
Date: 20241015

ACTIVE INGREDIENTS: NITROUS OXIDE 99 L/100 L

NITROUS OXIDE U.S.P. LABEL

NITROUS OXIDE USP UN1070
NON-FLAMMABLE GAS 2 DO NOT REMOVE THIS LABEL OXIDIZER 5.1

CONTENTS: _______________________________ LITERS ___ CU FT ____

Rx only.

WARNING: Administration of Nitrous Oxide may be hazardous or contraindicated. For use only by or under supervision of a licensed practitioner who is experienced in the use and administration of Nitrous Oxide and is familiar with the indications, effects, dosages, methods, and frequency and duration of administration, and with the hazards, contraindications, and side effects and the precautions to be taken.

WARNING: MAY CAUSE OR INTENSIFY FIRE; OXIDIZER. CONTAINS GAS UNDER PRESSURE; MAY EXPLODE IF HEATD. MAY CAUSE DROWSINESS OR DIZZINESS. MAY DISPLACE OXYGEN AND CAUSE RAPID SUFFOCATION. MAY CAUSE FROSTBITE.

Do not handle until all safety precautions have been read and understood. Keep and store away from clothing and other combustible materials. Keep valves and fitting free from grease and oil. Avoid breathing gas. Do not get in eyes, on skin, r on clothing. Use and store only outdoors or in a well-ventilated place. In case of fire; Stop leak if safe to do so. Use a back flow preventive device in the piping. Use only with equipment and compatible materials of construction and rated for cylinder pressure. Use only with equipment cleaned for oxygen service. Open valve slowly. Close valve after each use and when empty. Protect form sunlight when ambient temperature exceeds 52OC (125OF). Read and follow the Safety Data Sheet (SDS) before use.

FIRST AID: IF INHALED: Remove person to fresh air and keep comfortable for breathing. Call a POISON CENTER or doctor/physician if you feel unwell.

IF ON SKIN: Thaw frosted parts with lukewarm water. Do not rub affected area. Get immediate medical advice/attention.

WARNING: This product contains a chemical known to the state of California to cause birth defects or other reproductive harm.

CAS: 10024-97-2DO NOT REMOVE THIS PRODUCT LABEL.

In case of emergency involving this material call INFOTRAC at 1-800-535-5053

CRUMPTON WELDING SUPPLY & EQUIPMENT, INC.

1602 N 34TH STREET • TAMPA, FL 33605 • 800-229-6947

47736 (07/17)